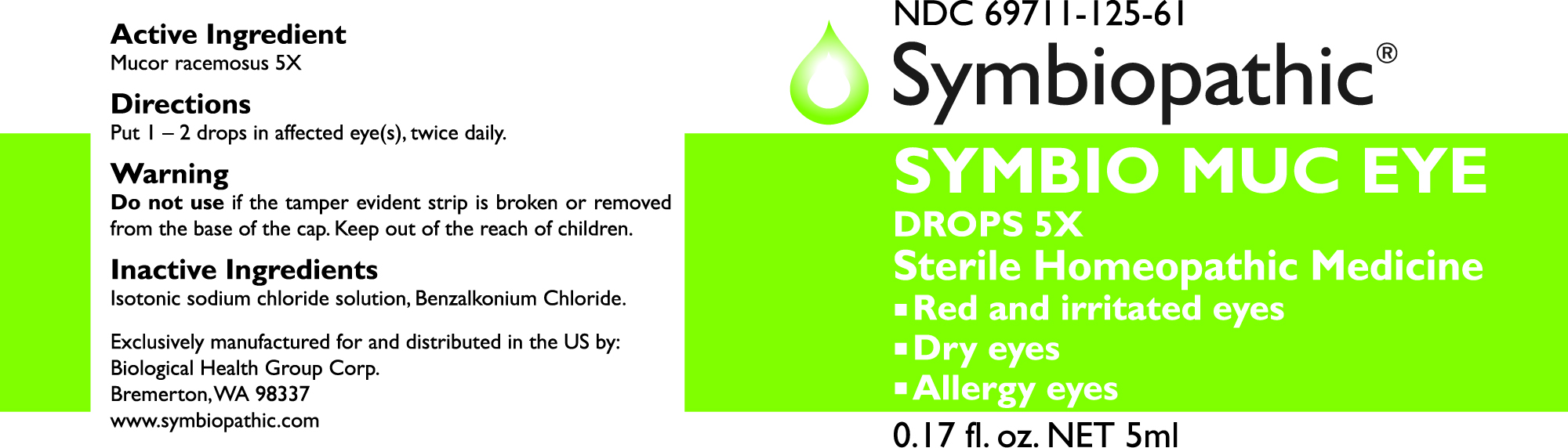 DRUG LABEL: SYMBIO MUC EYE DROPS
NDC: 69710-125 | Form: LIQUID
Manufacturer: Symbiopathic
Category: homeopathic | Type: HUMAN OTC DRUG LABEL
Date: 20251011

ACTIVE INGREDIENTS: MUCOR RACEMOSUS 5 [hp_X]/1 mL
INACTIVE INGREDIENTS: WATER; SODIUM CHLORIDE; BENZALKONIUM CHLORIDE

MUC 5X

ACTIVE INGREDIENTS:

Mucor racemosus 5X

WARNINGS:

Do not useif the tamper evident strip is broken or removed from the base of the cap.

• Contact lens wearers consult physician prior to using.

• To avoid contamination – do not touch tip to any surface.

• Replace cap after every use. • Use within 30 days of opening.

• EXPIRATION DATE ONLY REFERS TO THE UNOPENED BOTTLE.

• The use of this container by more than one person may spread infection.

DIRECTIONS:

Put 1 – 2 drops in affected eye(s), twice daily.

INACTIVE INGREDIENTS:

Purified water USP, sodium chloride

KEEP OUT OF REACH OF CHILDREN:In case of overdose, get medical help or call a Poison Control Center right away.

INDICATIONS:

This remedy is indicated for red and irritated eyes, dry eyes, and allergy eyes with burning and itching according to traditional homeopathic practice.*

QUESTIONS:

Call toll-free from US & CA +1-844-880-4881 or visit our website
www.biological-health.com

PURPOSE:

Irritated eyes.*

If pregnant or breast feeding, ask a health professional before use.

ASK DOCTOR:

Consult a physician if symptoms worsen or last for more than 7 days.

OTHER INFORMATION:

Protect from light and heat.

For professional distribution only.

*These statements are based upon traditional homeopathic practice. They have not been reviewed by the Food and Drug Administration.